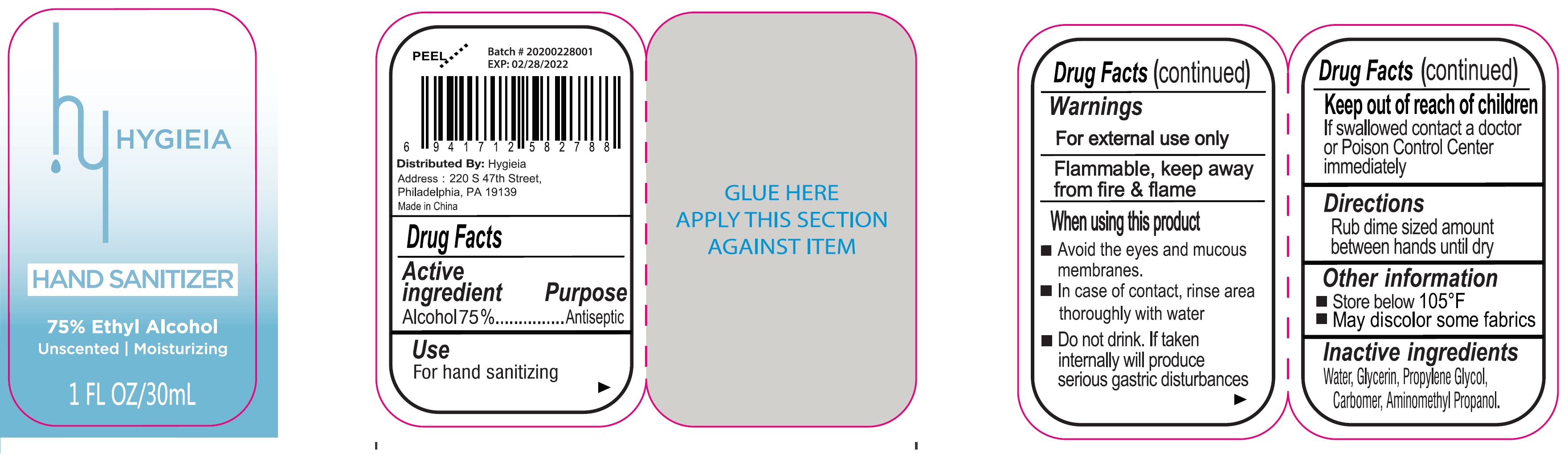 DRUG LABEL: hand sanitizer
NDC: 80689-000 | Form: GEL
Manufacturer: Hygieia
Category: otc | Type: HUMAN OTC DRUG LABEL
Date: 20231026

ACTIVE INGREDIENTS: ALCOHOL 0.75 mL/1 mL
INACTIVE INGREDIENTS: WATER; GLYCERIN; PROPYLENE GLYCOL; CARBOMER HOMOPOLYMER, UNSPECIFIED TYPE; AMINOMETHYLPROPANOL

hand sanitizer

Active ingredient

Alcohol 75%

Purpose

Antiseptic

Use

For hand sanitizing

Warnings

For external use only

Flammable, keep away from fire & flames.

When using this product

- Avoid the eyes and mucous membranes.
- In case of contact, rinse area thoroughly with water
- Do not drink. If taken internally will produce serious gastric disturbances

Keep out of reach of children

If swallowed contact a doctor or Poison Control Center immediately

Directions

Rub dime sized amount between hands until dry

Other information

- Store below 105 °F
- May discolor some fabrics

Inactive ingredients

Water, Glycerin, Propylene Glycol, Carbomer, Aminomethyl Propanol.